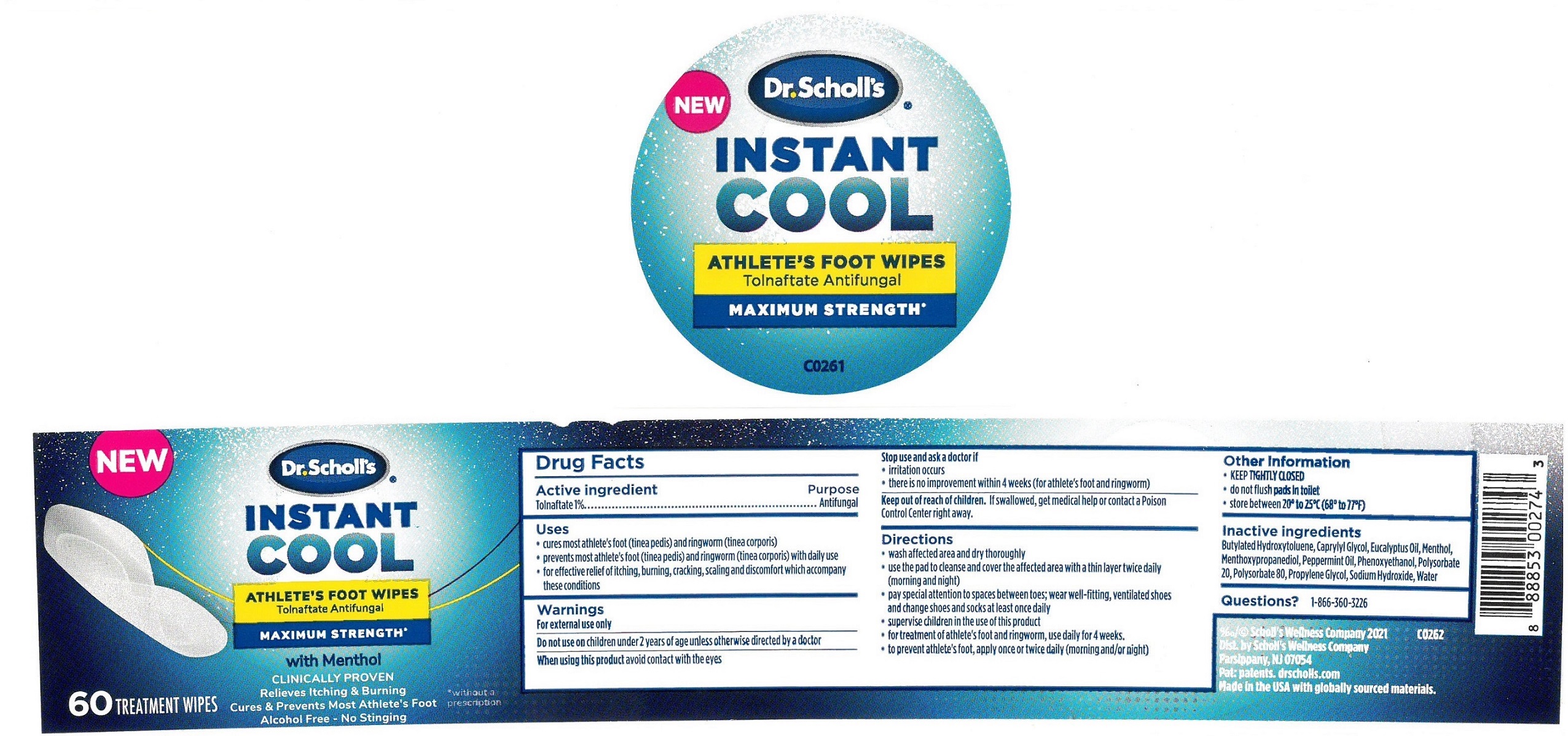 DRUG LABEL: Dr. Scholls Instant Cool Athletes Foot Wipes
NDC: 52261-8100 | Form: SWAB
Manufacturer: Cosco International, Inc.
Category: otc | Type: HUMAN OTC DRUG LABEL
Date: 20250206

ACTIVE INGREDIENTS: TOLNAFTATE 10 g/1000 g
INACTIVE INGREDIENTS: water; SODIUM HYDROXIDE; POLYSORBATE 80; POLYSORBATE 20; PROPYLENE GLYCOL; BUTYLATED HYDROXYTOLUENE; EUCALYPTUS OIL; 3-((L-MENTHYL)OXY)PROPANE-1,2-DIOL; menthol; PEPPERMINT OIL; PHENOXYETHANOL; CAPRYLYL GLYCOL

Active Ingredient

Tolnaftate 1%.........................Purpose: Antifungal

Purpose

Antifungal foot wipes

Uses

- cures most athlete's foot (tinea pedis) and ringworm (tinea corpois)
- prevents most athlete's foot (tinea pedis) and ringworm (tinea corpois) with daily use
- for effective relief of itching, burning, cracking, scaling, and discomfort which accompany these conditions

Warnings

For External use only

Do not use on children under 2 years of age unless otherwise directed by a doctor

When using this product avoid contact with the eyes

Stop use and ask a doctor if

- irritation occurs
- there is no improvement within 4 weeks (for athlete's foot and ringworm)

Keep out of reach of children. If swallowed, get medical help or contact a Poison Control Center right away.

Directions

- wash affected area and dry thoroughly
- use the pad to cleanse and cover the affected area with a thin layer twice daily (morning and night)
- pay special attention to spaces between toes; wear well-fitting, ventilated shoes and change shoes and socks at least once daily
- supervise children in the use of this product
- for treatment of athlete's foot and ringworm, use daily for 4 weeks.
- to prevent athlete's foot, apply once or twice daily (morning and/or night)

Other Information

- KEEP TIGHTLY CLOSED
- do not flush pads in toilet
- store between 20° ro 25°C (68° to 77°F)

Inactive ingredients

Butylated Hydroxytoluene, Caprylyl Glycol, Eucalyptus Oil, Menthol, Menthoxypropanediol, Peppermint Oil, Phenoxyethanol, Polysorbate 20, Polysorbate 80, Proylene Glycol, Sodium Hydroxide, Water

Questions? 1-866-360-3226